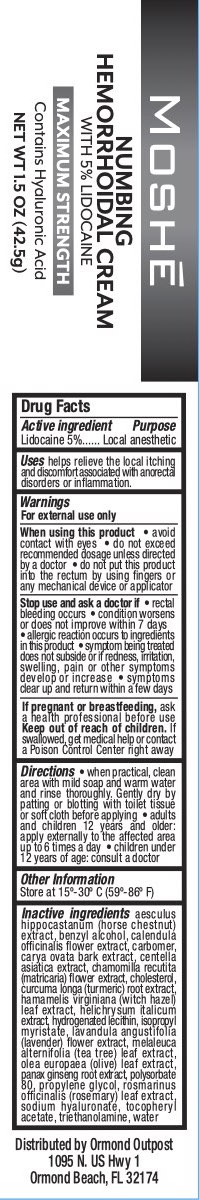 DRUG LABEL: Moshe Numbing Hemorrhoidal
NDC: 72839-218 | Form: CREAM
Manufacturer: Derma Care Research Labs
Category: otc | Type: HUMAN OTC DRUG LABEL
Date: 20241219

ACTIVE INGREDIENTS: LIDOCAINE 5 g/100 g
INACTIVE INGREDIENTS: HORSE CHESTNUT; ISOPROPYL MYRISTATE; PROPYLENE GLYCOL; WATER; TROLAMINE; .ALPHA.-TOCOPHEROL ACETATE; ASIAN GINSENG; LAVANDULA ANGUSTIFOLIA FLOWER; ROSEMARY; MATRICARIA CHAMOMILLA; HELICHRYSUM ITALICUM FLOWER; HYALURONIC ACID; MELALEUCA ALTERNIFOLIA LEAF; TURMERIC; HAMAMELIS VIRGINIANA LEAF; CARYA OVATA BARK; CALENDULA OFFICINALIS FLOWER; CENTELLA ASIATICA TRITERPENOIDS; OLEA EUROPAEA LEAF; BENZYL ALCOHOL; CARBOMER 940; POLYSORBATE 80; CHOLESTEROL; HYDROGENATED SOYBEAN LECITHIN

Moshe Hemorrhoidal Cream

ACTIVE INGREDIENT

Lidocaine 5.0%

PURPOSE

Local Anesthetic

Uses

Helps relieve the local itching and discomfort associated with anorectal disorders or inflammation.

WARNINGS

For external use only.

When using this product avoid contact with eyes, do not exceed recommended dosage unless directed by a doctor, do not put this product into the rectum by using fingers or any mechanical device or applicator.

Stop use and ask a doctor if rectal bleeding occurs, condition worsens or does not improve within 7 days, allergic reaction occurs to ingredients in this product, symptom being treated does not subside or if redness, irritation, swelling, pain or other symptoms develop or increase, or symptoms clear up and return within a few days.

PREGNANCY OR BREAST FEEDING

If pregnant or breastfeeding, ask a professional before use.

KEEP OUT OF REACH OF CHILDREN

Keep out of reach of the children. If swallowed, get medical help or contact a Poison Control Center right away.

DOSAGE AND ADMINISTRATION

- When practical, cleanse the area with mild soap and warm water. Rinse thoroughly and gently pat dry.
- Adults and children 12 years and older: apply externally to the affected area up to 6 times a day.
- Children under 12 years of age: consult a doctor.

INACTIVE INGREDIENT

Aesculus Hippocastanum (Horse Chestnut) Extract, Benzyl Alcohol, Calendula Officinalis Flower Extract, Carbomer, Carya Ovata Bark Extract, Centella Asiatica Extract, Chamomilla Recutita (Matricaria) Flower Extract, Cholesterol, Curcuma Longa (Turmeric) Root Extract, Hamamelis Virginiana (Witch Hazel) Leaf Extract, Helichrysum Italicum Extract, Hydrogenated Lecithin, Isopropyl Myristate, Lavandula Angustifolia (Lavender) Flower Extract, Melaleuca Alternifolia (Tea Tree) Leaf Extract, Olea Europaea (Olive) Leaf Extract, Panax Ginseng Root Extract, Polysorbate 80, Propylene Glycol, Rosmarinus Officinalis (Rosemary) Leaf Extract, Sodium Hyaluronate, Tocopheryl Acetate, Triethanolamine, Water.